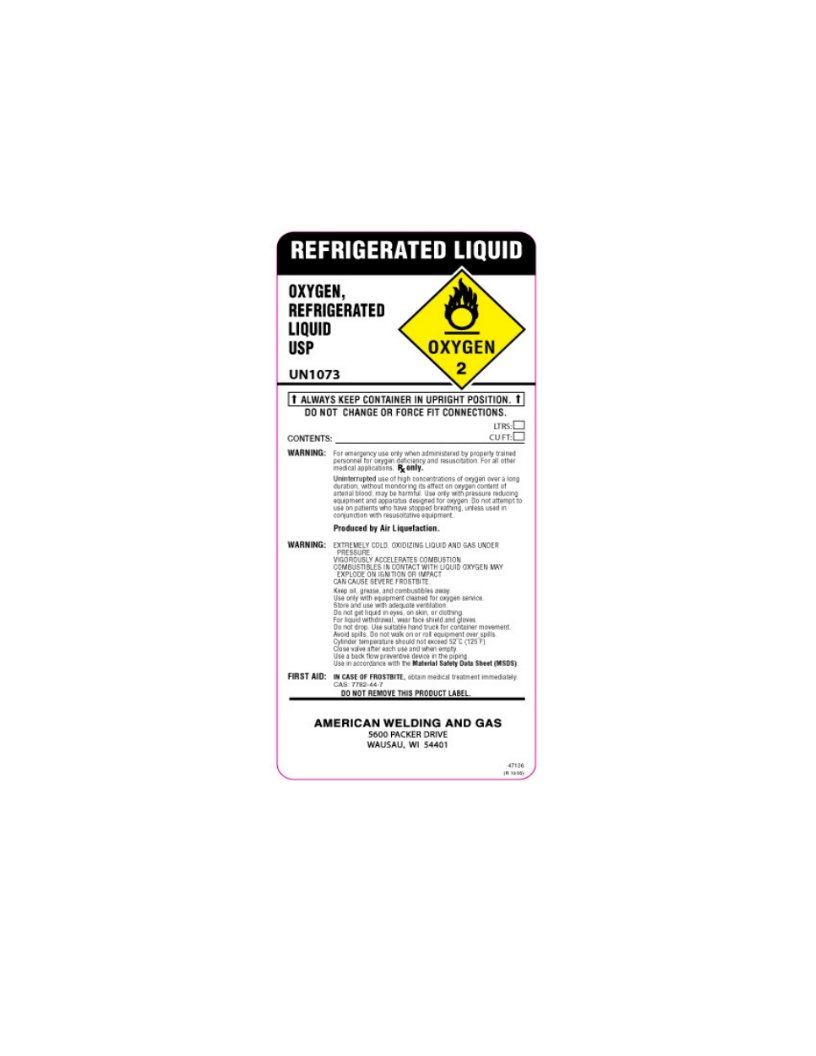 DRUG LABEL: Oxygen
NDC: 10825-002 | Form: GAS
Manufacturer: Northern Welding Supply
Category: prescription | Type: HUMAN PRESCRIPTION DRUG LABEL
Date: 20101001

ACTIVE INGREDIENTS: Oxygen 99 L/100 L

Liquid Oxygen Label

PACKAGE LABEL

OXYGEN,

REFRIGERATED LIQUID

USP

UN 1073
ALWAYS KEEP CONTAINER IN UPRIGHT POSITION.
DO NOT CHANGE OR FORCE FIT CONNECTIONS.
CONTENTS: LTRS:_____, CU FT:_____
WARNING: For emergency use only when administered by properly trained personnel for oxygen deficiency and resuscitation. For all other medical applications, Rx only. Uninterrupted use of high concentrations of oxygen over a long duration, without monitoring its effect on oxygen content of arterial blood, may be harmful. Use only with pressure reducing equipment and apparatus designed for oxygen. Do not attempt to use on patients who have stopped breathing, unless used in conjunction with resuscitative equipment.
Produced by Air Liquefaction.
WARNING: EXTREMELY COLD, OXIDIZING LIQUID AND GAS UNDER PRESSURE, VIGOROUSLY ACCELERATES COMBUSTION. COMBUSTABLES IN CONTACT WITH LIQUID OXYGEN MAY EXPLODE ON IGNITION OR IMPACT CAN CAUSE SEVER FROSTBITE.
Keep oil, grease, and combustibles away.
Use only with equipment cleaned for oxygen service.
Store and use with adequate ventilation.
Do not get liquid in eyes, on skin, or clothing.
for liquid withdrawal, wear face shield and gloves.
Do not drop. Use suitable hand truck for container movement.
Avoid spills. Do not walk on or roll equipment over spills.
Cylinder temperature should not exceed 52C (125F).
Close valve after each use and when empty.
Use a back flow preventive device in the piping.
Use in accordance with the Material Safety Data Sheet (MSDS).
FIRST AID: IN CASE OF FROSTBITE, obtain medical treatment immediately.
DO NOT REMOVE THIS PRODUCT LABEL.
AMERICAN WELDING AND GAS
5600 PACKER DRIVE
WAUSAU, WI 54401